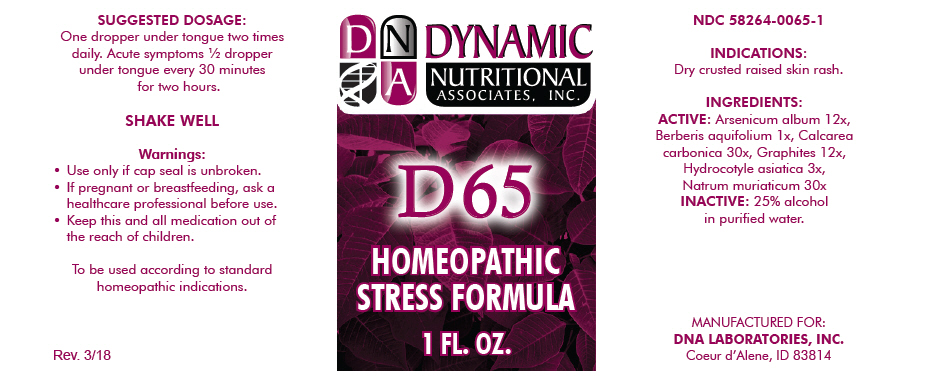 DRUG LABEL: D-65
NDC: 58264-0065 | Form: SOLUTION
Manufacturer: DNA Labs, Inc.
Category: homeopathic | Type: HUMAN OTC DRUG LABEL
Date: 20250113

ACTIVE INGREDIENTS: ARSENIC TRIOXIDE 12 [hp_X]/1 mL; BERBERIS AQUIFOLIUM ROOT BARK 1 [hp_X]/1 mL; OYSTER SHELL CALCIUM CARBONATE, CRUDE 30 [hp_X]/1 mL; GRAPHITE 12 [hp_X]/1 mL; CENTELLA ASIATICA 3 [hp_X]/1 mL; SODIUM CHLORIDE 30 [hp_X]/1 mL
INACTIVE INGREDIENTS: ALCOHOL; WATER

D-65

NDC 58264-0065-1

INDICATIONS

PURPOSE

Dry crusted raised skin rash.

INGREDIENTS

ACTIVE

Arsenicum album 12x, Berberis aquifolium 1x, Calcarea carbonica 30x, Graphites 12x, Hydrocotyle asiatica 3x, Natrum muriaticum 30x

INACTIVE

25% alcohol in purified water.

SUGGESTED DOSAGE

One dropper under tongue two times daily. Acute symptoms ½ dropper under tongue every 30 minutes for two hours.

STORAGE AND HANDLING

SHAKE WELL

Warnings

- Use only if cap seal is unbroken.

PREGNANCY OR BREAST FEEDING

- If pregnant or breastfeeding, ask a healthcare professional before use.

KEEP OUT OF REACH OF CHILDREN

- Keep this and all medication out of the reach of children.

To be used according to standard homeopathic indications.

PRINCIPAL DISPLAY PANEL - 1 FL. OZ. Bottle Label

DYNAMIC
NUTRITIONAL
ASSOCIATES, INC.

D 65

HOMEOPATHIC
STRESS FORMULA

1 FL. OZ.